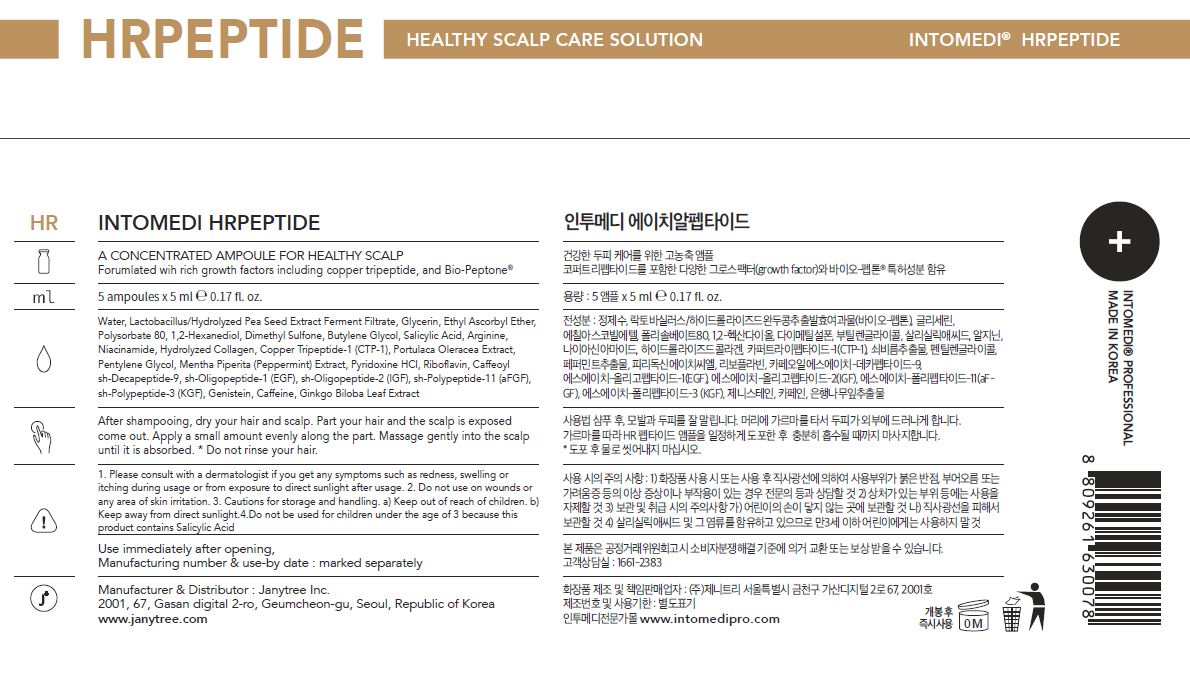 DRUG LABEL: INTOMEDI HR PEPTIDE
NDC: 82879-0007 | Form: LIQUID
Manufacturer: Janytree Inc.
Category: otc | Type: HUMAN OTC DRUG LABEL
Date: 20220712

ACTIVE INGREDIENTS: NIACINAMIDE 0.3 g/100 mL
INACTIVE INGREDIENTS: BUTYLENE GLYCOL; WATER; GLYCERIN

INACTIVE INGREDIENTS

Water, Lactobacillus/Hydrolyzed Pea Seed Extract Ferment Filtrate, Glycerin, Ethyl Ascorbyl Ether,
Polysorbate 80, 1,2-Hexanediol, Dimethyl Sulfone, Butylene Glycol, Salicylic Acid, Arginine,
Hydrolyzed Collagen, Copper Tripeptide-1 (CTP-1), Portulaca Oleracea Extract,
Pentylene Glycol, Mentha Piperita (Peppermint) Extract, Pyridoxine HCl, Riboflavin, Caffeoyl
sh-Decapeptide-9, sh-Oligopeptide-1 (EGF), sh-Oligopeptide-2 (IGF), sh-Polypeptide-11 (aFGF),
sh-Polypeptide-3 (KGF), Genistein, Caffeine, Ginkgo Biloba Leaf Extract

ACTIVE INGREDIENTS

Niacinamide

PURPOSE

A CONCENTRATED AMPOULE FOR HEALTHY SCALP
Forumlated wih rich growth factors including copper tripeptide, and Bio-Peptone®

WARNINGS

For external use only When using this product
■ If following abnormal symptoms occurs after using the product, stop using the product and consult with a skin specialist. Symptoms : Red specks, swelling, itching
■ Do not use on the skin parts affected by wound, eczema, or dermatitis.
Keep out of reach of children.
■ If swallowed, get a medical help or contact a person in control center immediately.
■ Avoid contact with eyes.

KEEP OUT OF REACH OF CHILDREN

If swallowed, get a medical help or contact a person in control center immediately.

INDICATIONS AND USAGE

After shampooing, dry your hair and scalp. Part your hair and the scalp is exposed
come out. Apply a small amount evenly along the part. Massage gently into the scalp
until it is absorbed. * Do not rinse your hair.

DOSAGE AND ADMINISTRATION

for external use only